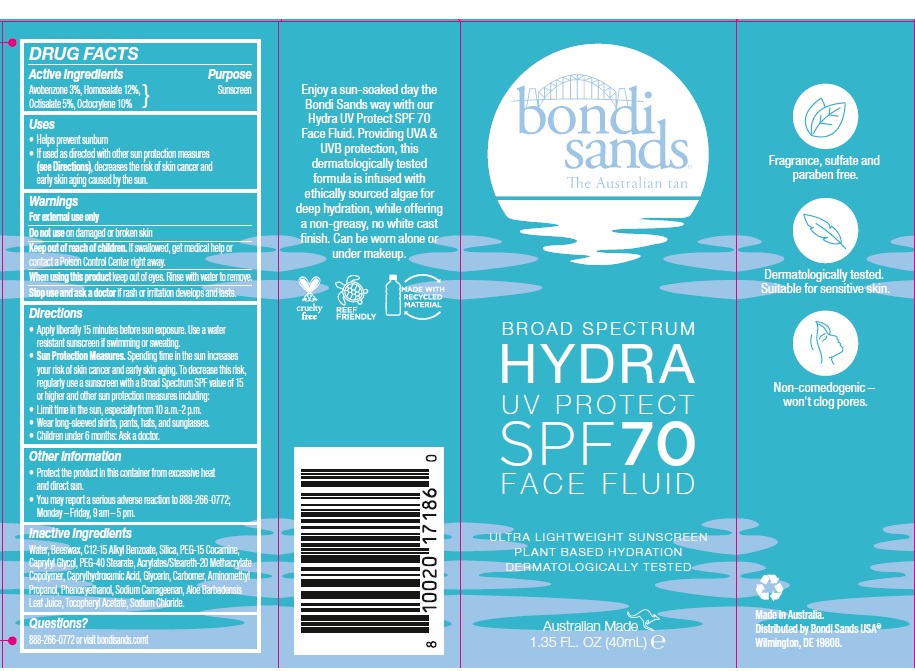 DRUG LABEL: Bondi Sands Broad Spectrum Hydra UV Protect SPF 70 Face Fluid
NDC: 70157-019 | Form: LOTION
Manufacturer: Baxter Laboratories Pty. Ltd.
Category: otc | Type: HUMAN OTC DRUG LABEL
Date: 20240126

ACTIVE INGREDIENTS: AVOBENZONE 30 mg/1 mL; OCTOCRYLENE 100 mg/1 mL; HOMOSALATE 120 mg/1 mL; OCTISALATE 50 mg/1 mL
INACTIVE INGREDIENTS: CAPRYLHYDROXAMIC ACID; PHENOXYETHANOL; CARBOMER HOMOPOLYMER, UNSPECIFIED TYPE; ALKYL (C12-15) BENZOATE; SILICON DIOXIDE; WATER; ALOE VERA LEAF; .ALPHA.-TOCOPHEROL ACETATE; PEG-15 COCAMINE; CARRAGEENAN; YELLOW WAX; AMINOMETHYLPROPANOL; GLYCERIN; SODIUM CHLORIDE; ETHYL ACRYLATE/METHACRYLIC ACID/STEARETH-20 METHACRYLATE COPOLYMER; PEG-40 STEARATE; CAPRYLYL GLYCOL

Bondi Sands Broad Spectrum Hydra UV Protect SPF 70 Face Fluid

Active Ingredients

Avobenzone 3%, Homosalate 12%, Octisalate 5%, Octocrylene 10%

Purpose

Sunscreen

Uses

- Helps prevent sunburn
- If used as directed with other sun protection measures (see Directions), decreases the risk of skin cancer and early skin aging caused by the sun.

Warnings

For external use only

Do not use on damaged or broken skin.

Stop use and ask a doctor if rash occurs.

Keep out of reach of children.

If swallowed, get medical help or contact a Poison Control Center right away.

When using this product

keep out of eyes. Rinse with water to remove.

Directions

- Apply liberally 15 minutes before sun exposure. Use a water resistant sunscreen if swimming or sweating.
- Sun Protection Measures. Spending time in the sun increases your risk of skin cancer and early skin aging. To decrease this risk, regularly use a sunscreen with a Broad Spectrum SPF value of 15 or higher and other sun protection measures including:
- Limit time in the sun, especially from 10 a.m.- 2 p.m.
- Wear long-sleeved shirts, pants, hats, and sunglasses.
- Children under 6 months: Ask a doctor.

Other information

- Protect the product in this container from excessive heat and direct sun.
- You may report a serious adverse reaction to 888-266-0772; Monday – Friday, 9 am – 5 pm.

Inactive Ingredients

Water, Beeswax, C12-15 Alkyl Benzoate, Silica, PEG-15 Cocamine, Caprylyl Glycol, PEG-40 Stearate, Acrylates/Steareth-20 Methacrylate Copolymer, Caprylhydroxamic Acid, Glycerin, Carbomer, Aminomethyl Propanol, Phenoxyethanol, Sodium Carrageenan, Aloe Barbadensis Leaf Juice, Tocopheryl Acetate, Sodium Chloride.

Questions?

888-266-0772 or visit bondisands.com

Product Packaging

bondi sands

The Australian tan

BROAD SPECTRUM

HYDRA

UV PROTECT

SPF 70

FACE FLUID

ULTRA LIGHTWEIGHT SUNSCREEN

PLANT BASED HYDRATION

DERMATOLOGICALLY TESTED

Australian Made

1.35 FL. OZ. (40 mL)